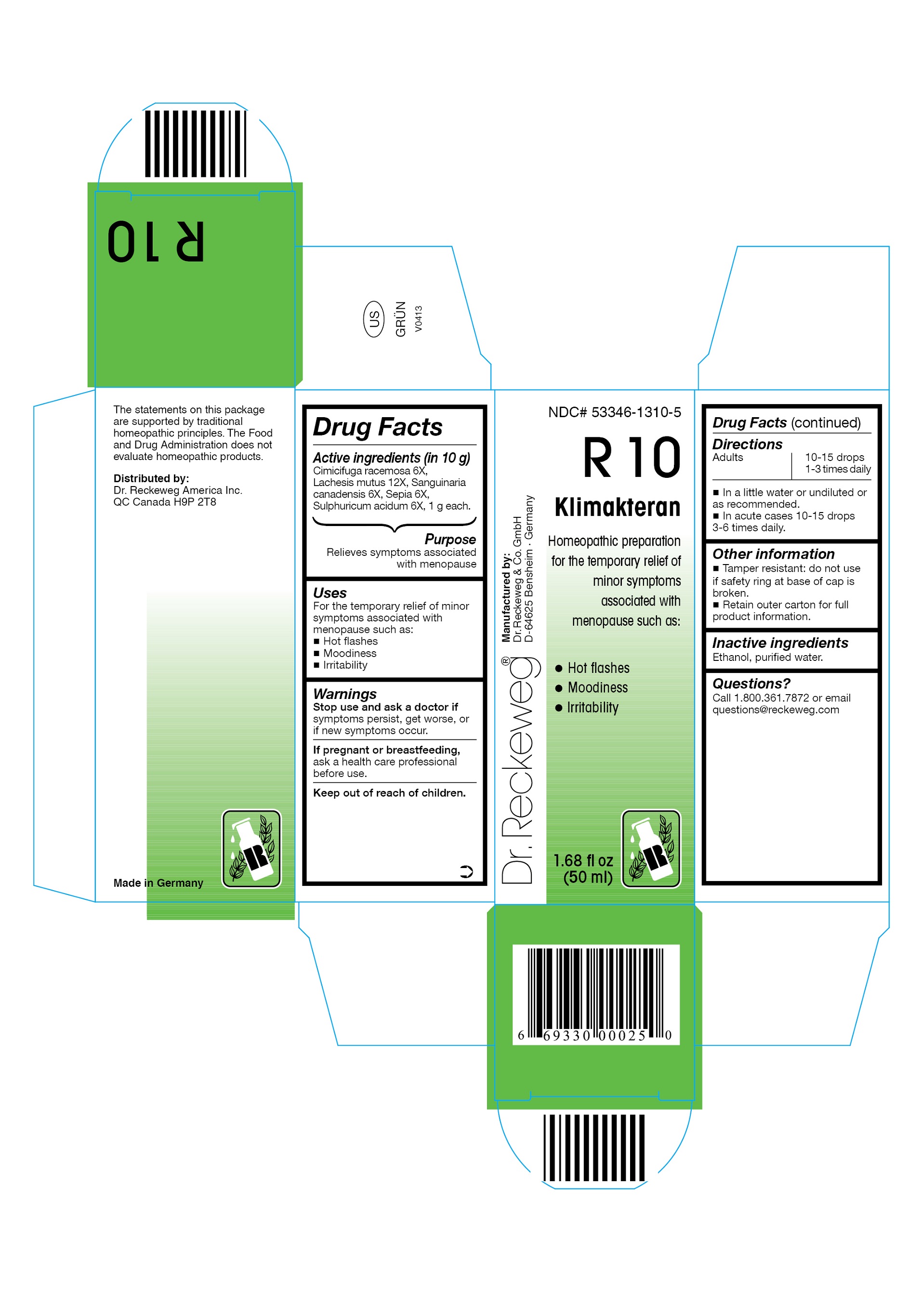 DRUG LABEL: Dr. Reckeweg R10 Klimakteran
NDC: 53346-1310 | Form: LIQUID
Manufacturer: PHARMAZEUTISCHE FABRIK DR. RECKEWEG & CO
Category: homeopathic | Type: HUMAN OTC DRUG LABEL
Date: 20130403

ACTIVE INGREDIENTS: BLACK COHOSH 6 [hp_X]/50 mL; LACHESIS MUTA VENOM 12 [hp_X]/50 mL; SANGUINARIA CANADENSIS ROOT 6 [hp_X]/50 mL; SEPIA OFFICINALIS JUICE  6 [hp_X]/50 mL; SULFURIC ACID 6 [hp_X]/50 mL
INACTIVE INGREDIENTS: ALCOHOL; WATER

Dr. Reckeweg R10 Klimakteran

Active ingredients

Cimicifuga racemosa 6X, Lachesis mutus 12X, Sanguinaria canadensis 6X, Sepia 6X, Sulphuricum acidum 6X, 1 g each in 10 g.

Purpose

Relieves symptoms associated with menopause

Uses

For the temporary relief of minor symptoms associated with menopause such as:

- Hot flashes
- Moodiness
- Irritability

Warnings

Stop use and ask a doctor if symptoms persist, get worse, or if new symptoms occur.

PREGNANCY OR BREAST FEEDING

If pregnant or breastfeeding, ask a health care professional before use.

Keep out of reach of children.

Directions
Adults: 10-15 drops 1-3 times daily;

acute cases: 10-15 drops 3-6 times daily in a little water or undiluted or as recommended.

Other information

- Tamper resistant: do not use if safety ring at base of cap is broken.
- Retain outer carton for full product Information.

Inactive ingredients

Ethanol, purified water.

Questions?

Call 1-800-361-7872 or email questions@reckeweg.com

PACKAGE LABEL

NDC# 53346-1310-5

Dr. Reckeweg R10 Klimakteran

Homeopathic preparation for the temporary relief of minor symptoms associated with menopause such as:

- Hot flashes
- Moodiness
- Irritability

Manufactured by:

Dr. Reckeweg Co. GmbH

D-64625 Bensheim

Germany

1.68 fl oz
(50 ml)